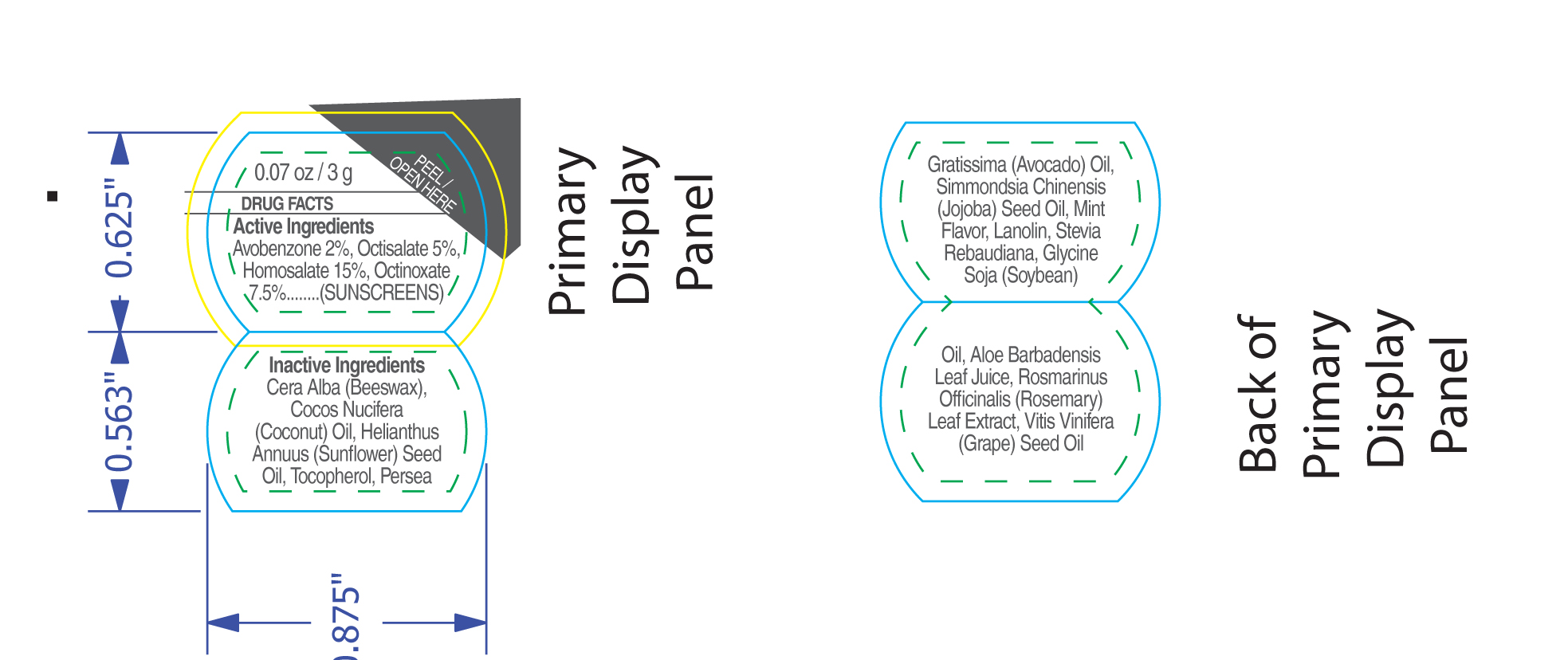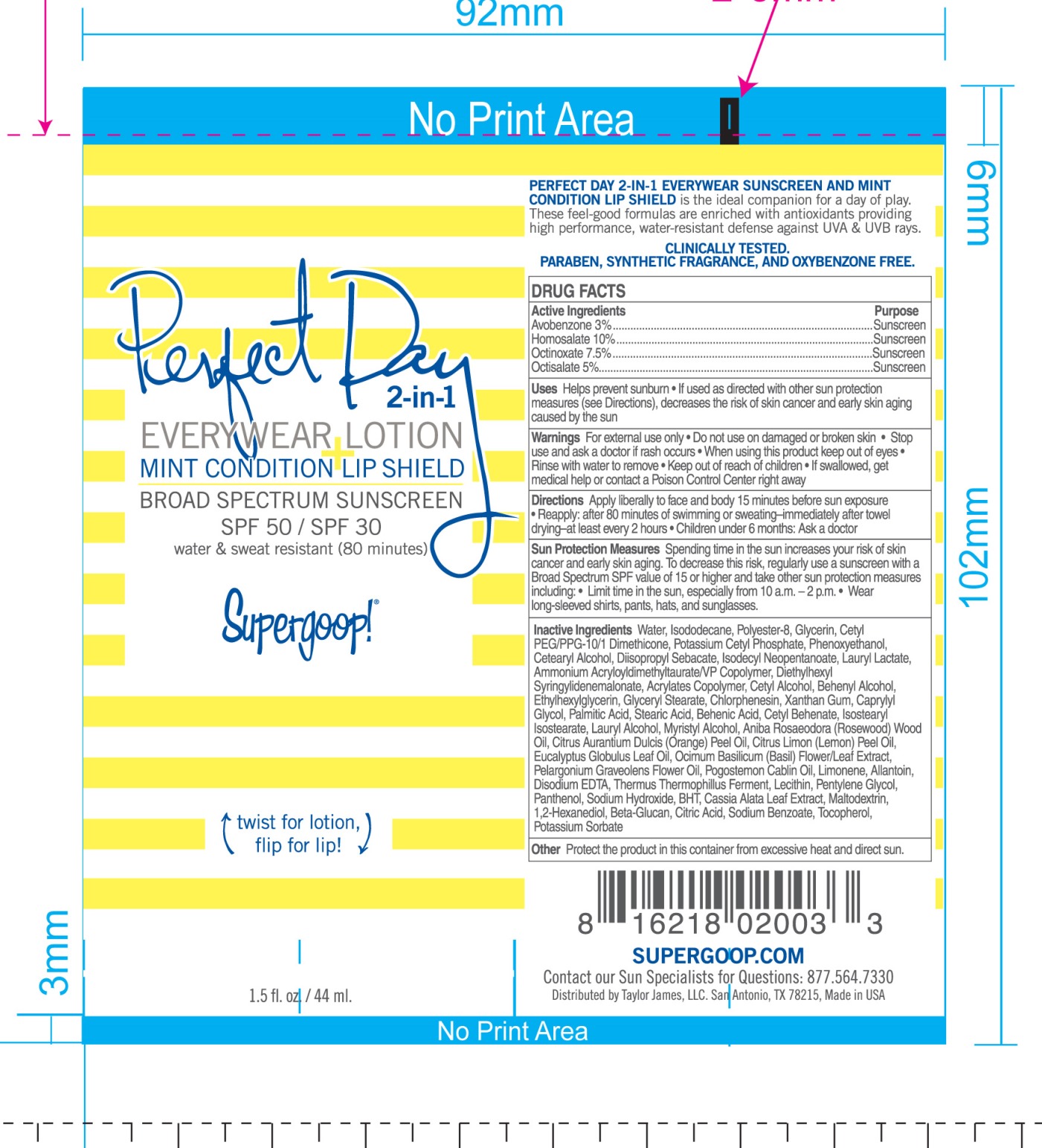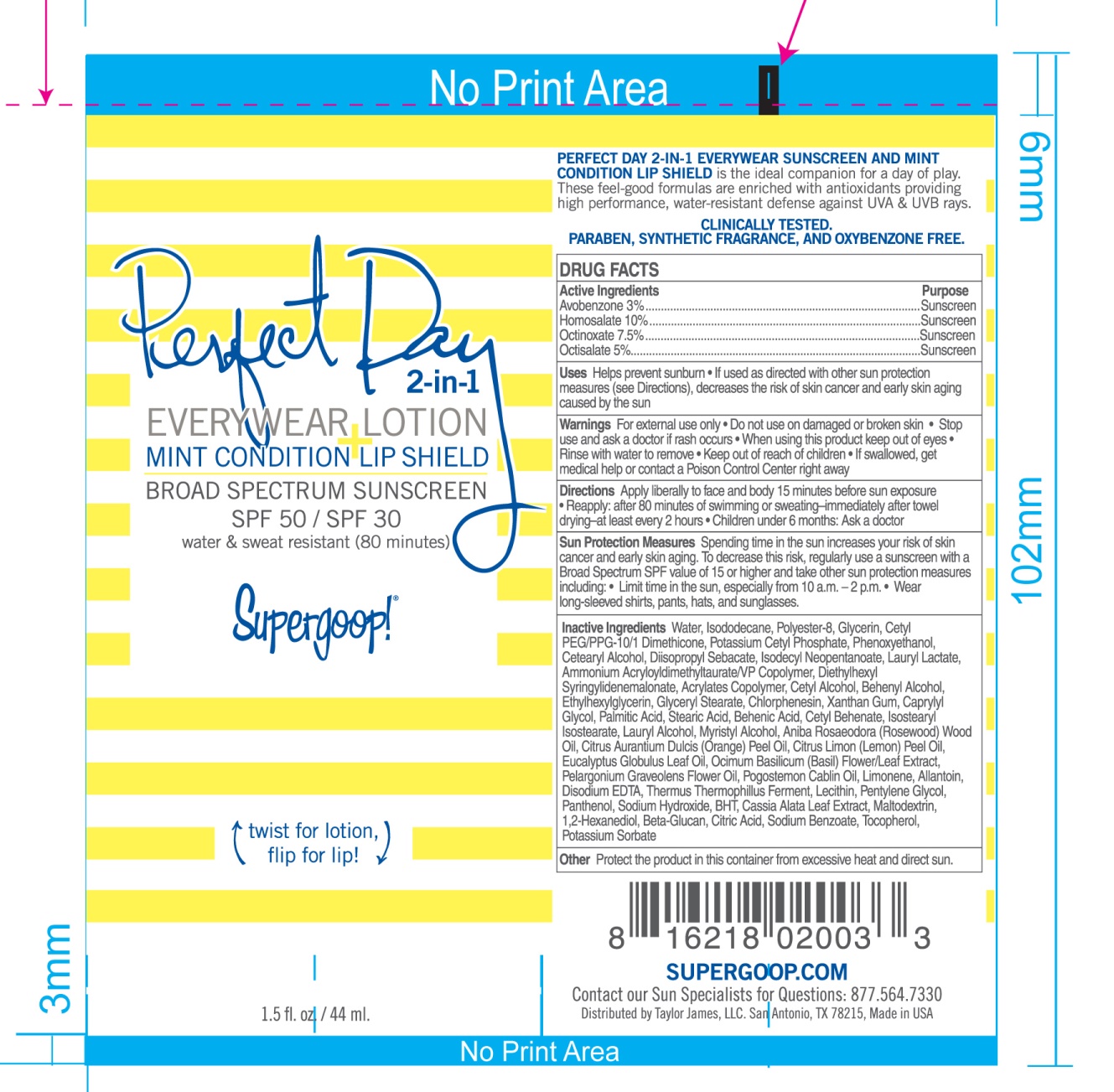 DRUG LABEL: Perfect Day 2 in 1 Everywear SPF 50 and Mint Condition Lip Shield SPF 30
NDC: 75936-500 | Form: KIT | Route: TOPICAL
Manufacturer: TAYLOR JAMES, LTD.
Category: otc | Type: HUMAN OTC DRUG LABEL
Date: 20170116

ACTIVE INGREDIENTS: AVOBENZONE 3 g/100 mL; HOMOSALATE 10 g/100 mL; OCTINOXATE 7.5 g/100 mL; OCTISALATE 5 g/100 mL; AVOBENZONE 2 g/100 g; OCTISALATE 5 g/100 g; HOMOSALATE 15 g/100 g; OCTINOXATE 7.5 g/100 g
INACTIVE INGREDIENTS: WATER; ISODODECANE; POLYESTER-8 (1400 MW, CYANODIPHENYLPROPENOYL CAPPED); GLYCERIN; CETYL PEG/PPG-10/1 DIMETHICONE (HLB 1.5); POTASSIUM CETYL PHOSPHATE; PHENOXYETHANOL; CETOSTEARYL ALCOHOL; DIISOPROPYL SEBACATE; ISODECYL NEOPENTANOATE; LAURYL LACTATE; AMMONIUM ACRYLOYLDIMETHYLTAURATE/VP COPOLYMER; DIETHYLHEXYL SYRINGYLIDENEMALONATE; CETYL ALCOHOL; DOCOSANOL; ETHYLHEXYLGLYCERIN; GLYCERYL MONOSTEARATE; CHLORPHENESIN; XANTHAN GUM; CAPRYLYL GLYCOL; PALMITIC ACID; STEARIC ACID; BEHENIC ACID; CETYL BEHENATE; ISOSTEARYL ISOSTEARATE; LAURYL ALCOHOL; MYRISTYL ALCOHOL; ROSEWOOD OIL; ORANGE OIL; LEMON OIL; EUCALYPTUS OIL; OCIMUM BASILICUM FLOWERING TOP; PELARGONIUM GRAVEOLENS FLOWER OIL; PATCHOULI OIL; ALLANTOIN; EDETATE DISODIUM; THERMUS THERMOPHILUS LYSATE; LECITHIN, SOYBEAN; PENTYLENE GLYCOL; PANTHENOL; SODIUM HYDROXIDE; BUTYLATED HYDROXYTOLUENE; SENNA ALATA LEAF; MALTODEXTRIN; 1,2-HEXANEDIOL; CITRIC ACID MONOHYDRATE; SODIUM BENZOATE; TOCOPHEROL; POTASSIUM SORBATE; WHITE WAX; COCONUT OIL; SUNFLOWER OIL; TOCOPHEROL; AVOCADO OIL; JOJOBA OIL; LANOLIN; STEVIA REBAUDIUNA LEAF; SOYBEAN OIL; ALOE VERA LEAF; ROSEMARY; GRAPE SEED OIL

Perfect Day 2-in-1 Broad Spectrum Sunscreen Everywear Lotion SPF 50 + Mint Condition Lip Shield SPF 30

ACTIVE INGREDIENT

Lotion

Active Ingredients Purpose

Avobenzone 3% ...................... Sunscreen

Homosalate 10% ..................... Sunscreen

Octinoxate 7.5% ...................... Sunscreen

Octisalate 5% .......................... Sunscreen

Lip Shield

Active Ingredients Purpose

Avobenzone 2% ...................... Sunscreen

Homosalate 15% ..................... Sunscreen

Octinoxate 7.5% ...................... Sunscreen

Octisalate 5% .......................... Sunscreen

Uses

- Helps prevent sunburn
- If used as directed with other sun protection measures (see Directions), decreases the risk of skin cancer and early skin aging caused by the sun

Keep out of reach of children

Stop use and ask a doctor if rash occurs

Warnings

- For external use only
- Do not use on damaged or broken skin
- When using this product keep out of eyes
- Rinse with water to remove
- If Swallowed, get medical help or contact a Poison Control Center right away

Directions

- Apply liberally to face and body 15 minutes before sun exposure
- Reapply: after 80 minutes of swimming or sweating-immediately after towel drying-at least every 2 hours
- Children under 6: Ask a doctor

Suns Protection Measures Spending time in the sun increases your risk of skin cancer an early skin aging. To decrease this risk, regularly use a sunscreen with a Broad Spectrum SPF value of 15 or higher and take other sun protection measures including:

- Limit time in the sun, especially from 10 a.m. - 2 p.m.
- Wear long-sleeved shirts, pants, hats, and sunglasses

INACTIVE INGREDIENT

Lotion

Water, Isododecane, Polyester-8, Glycerin, Cetyl PEG/PPG-10/1 Dimethicone, Potassium Cetyl Phosphate, Phenoxyethanol, Cetearyl Alcohol, Diisopropyl Sebacate, Isodecyl Neopentanoate, Lauryl Lactate, Ammonium Acyloyldimethyltaurate/VP Copolymer, Diethylhexyl Syringylidenemalonate, Acyrlates Copolymer, Cetyl Alcohol, Behenyl Alcohol, Ethyhexylglycerin, Glyceryl Stearate, Chlorphenesin, Xanthan Gum, Caprylyl Glycol, Pamitic Acid, Stearic Acid, Behenic Acid, Cetyl Behenate, Isostearyl Isostearate, Lauryl Alcohol, Myristyl Alcohol, Aniba Rosaedora (Rosewood) Wood Oil, Citrus Aurantium Dulcis (Orange) Peel Oil, Citrus Limon (Lemon) Peel Oil, Eucalyptus Globulus Leaf Oil, Ocimum Basilicum (Basil) Flower/Leaf Extract, Pelargonium Graveolens Flower Oil, Pogostemon Cabin Oil, Limonene, Allantoin, Disodium EDTA, Thermus Thermophillus Ferment, Lecithin, Pentylene Glycol, Panthenol, Sodium Hydorxide, BHT, Cassia Alata Leaf Extract, Maltodextrin, 1,2-Hexanediol, Beta-Glucan, Citric Acid, Sodium Benzoate, Tocopherol, Potassium Sorbate

Lip Shield

Coera Alba (Beeswax), Cocos Nucifera (Coconut) Oil, Helianthus Anuus (Sunflower) Seed Oil, Tocopherol, Persea Gratissima (Avocado) Oil, Simmondsia Chinensis (Jojoba) Seed Oil, Mint Flavor, Lanolin, Stevia Rebaudiana, Glycine Soja (Soybean) Oil, Aloe Barbadensis Leaf Juice, Rosmarinus Officinalis (Rosemary) Leaf Extract, Vitis Vinifera (Grape) Seed Oil

PACKAGE LABEL

Perfect Day 2-in-1

Everywear Lotion + Mint Codnitions Lipshield

Broad Spectrum Sunscreen SPF 50/ SPF 30

1.5 fl. oz. / 44 ml

0.07oz / 3g